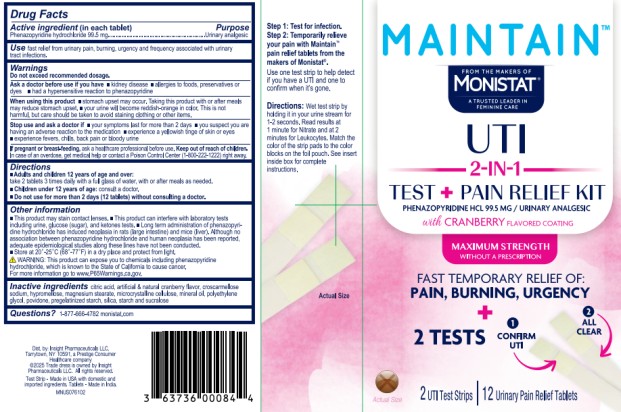 DRUG LABEL: Monistat Maintain
NDC: 63736-020 | Form: TABLET
Manufacturer: Insight Pharmaceuticals LLC
Category: otc | Type: HUMAN OTC DRUG LABEL
Date: 20251023

ACTIVE INGREDIENTS: PHENAZOPYRIDINE HYDROCHLORIDE 99.5 mg/1 1
INACTIVE INGREDIENTS: CITRIC ACID; CROSCARMELLOSE SODIUM; HYPROMELLOSES; MAGNESIUM STEARATE; CELLULOSE, MICROCRYSTALLINE; MINERAL OIL; POLYETHYLENE GLYCOL, UNSPECIFIED; POVIDONE; SILICON DIOXIDE; STARCH, CORN; SUCRALOSE

Monistat Maintain 63736-020-12

Drug Facts

Active ingredient (in each tablet)

Phenazopyridine hydrochloride 99.5 mg

Purpose

Urinary analgesic

Use

fast relief from urinary pain, burning, urgency and frequency associated with urinary tract infections

Warnings

Ask a doctor before use if you have

- kidney disease
- allergies to foods, preservatives, or dyes
- had a hypersensitive reaction to phenazopyridine

When using this product

- stomach upset may occur. Taking this product with or after meals may reduce stomach upset.
- your urine will become reddish-orange in color. This is not harmful, but care should be taken to avoid staining clothing or other items.

Stop use and ask a doctor if

- your symptoms last for more than 2 days
- you suspect you are having an adverse reaction to the medication
- experience a yellowish tinge of skin or eyes
- experience fevers, chills, back pain or bloody urine

If pregnant or breast feeding,

ask a healthcare professional before use.

Keep out of reach of children.

In case of an overdose, get medical help or contact a Poison Control Center (1-800-222-1222) right away.

Directions

- Adults and children 12 years of age and over: take 2 tablets 3 times daily with a full glass of water, with or after meals as needed.
- Children under 12 years of age: consult a doctor.

Do not use for more than 2 days (12 tablets) without consulting a doctor.

Other information

- This product may stain contact lenses.
- This product can interfere with laboratory tests including urine, glucose (sugar), and ketones tests.
- Long term administration of phenazopyridine hydrochloride has induced neoplasia in rats (large intestine) and mice (liver). Although no association between phenazopyridine hydrochloride and human neoplasia has been reported, adequate epidemiological studies along these lines have not been conducted.
- Store at 20º-25º C (68º-77º F) in a dry place and protect from light.

WARNING: This product can expose you to chemicals including phenazopyridine hydrochloride, which is known to the State of California to cause cancer. For more information go to www.P65Warnings.ca.gov.

Inactive ingredients

citric acid, artificial & natural cranberry flavor, croscarmellose sodium, hypromellose, magnesium stearate, microcrystalline cellulose, mineral oil, polyethylene glycol, povidone, pregelatinized starch, silica, starch, and sucralose

Questions?

1-877-666-4782 monistat.com

PRINCIPAL DISPLAY PANEL

Maintain™ from the makers of Monistat® A Trusted Leader In Feminine Care (Logo)

UTI

2-in-1

TEST + PAIN RELIEF KIT

Phenazopyridine HCl 99.5 mg / Urinary analgesic

with CRANBERRY FLAVORED COATING

2 UTI Test Strips | 12 Urinary Pain Relief Tablets